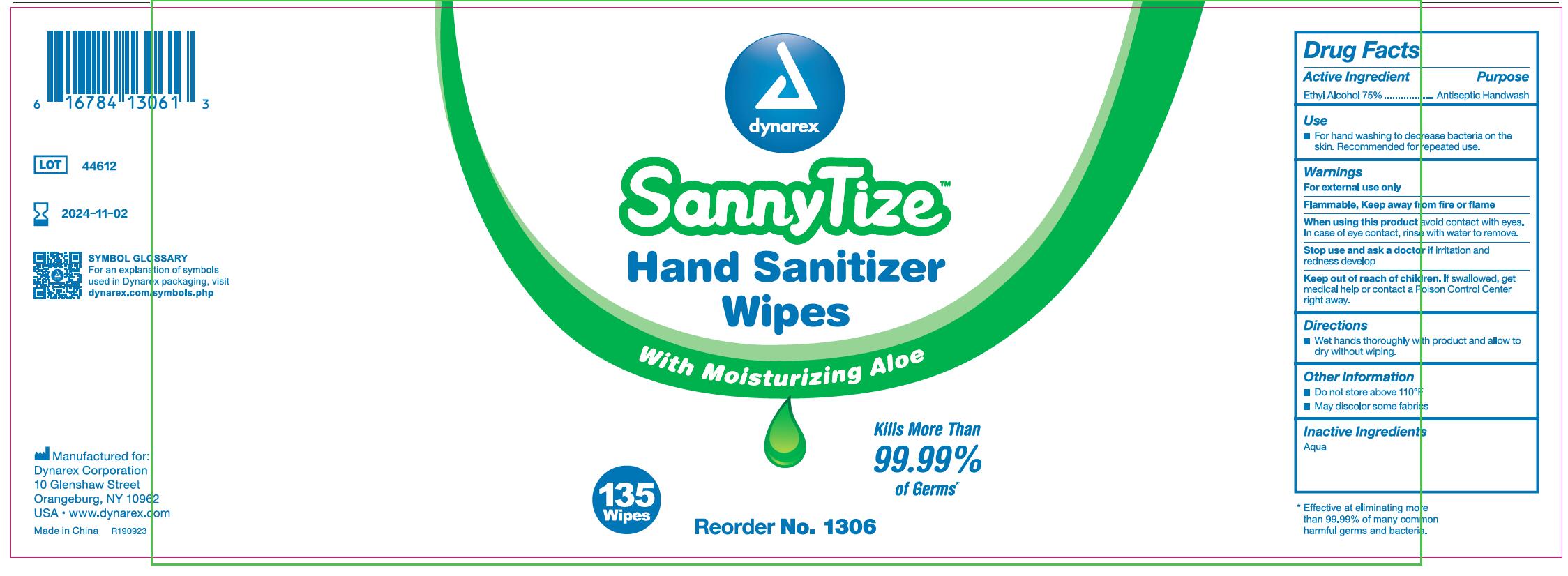 DRUG LABEL: Hand Sanitizer Wipes
NDC: 78411-003 | Form: CLOTH
Manufacturer: Zhejiang Qirun Daily Necessities Co., Ltd.
Category: otc | Type: HUMAN OTC DRUG LABEL
Date: 20200613

ACTIVE INGREDIENTS: ALCOHOL 75 g/100 g
INACTIVE INGREDIENTS: WATER

78411-003 wet wipes 75% Ethyl Alcohol

Active Ingredient

Ethyl Alcohol 75%

Purpose

Antiseptic Handwash

USE

For hand washing to decrease bacteria on the skin.
Recommended for repeated use.

Warning

For external use only
Flammable - Keep away from fire or flame
When using this product, avoid contact with eyes. In case of
eye contact, rinse with water to remove.
Stop use and ask a doctor if irritation and redness develop.

Keep out of reach of children. If swallowed, get medical help
or contact a Poison Control Center right away.

Directions

. Wet hands thoroughly with product and allow to dry without wiping.

Inactive ingredients

Aqua